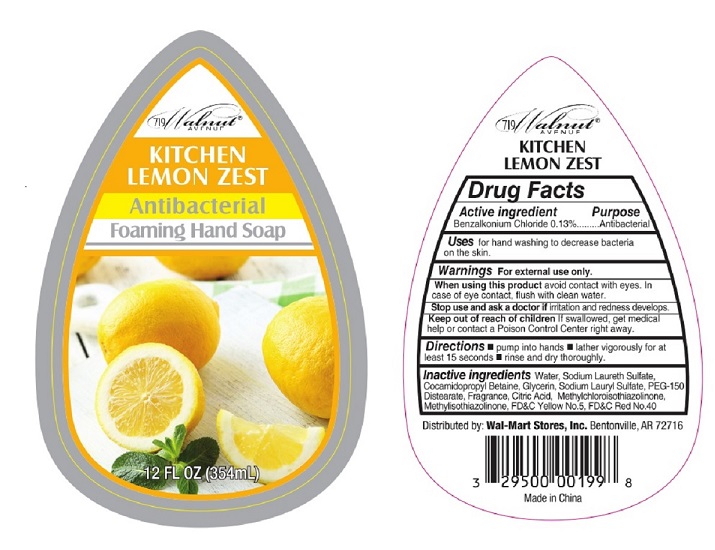 DRUG LABEL: KITCHEN LEMON ZEST
NDC: 29500-9882 | Form: LIQUID
Manufacturer: GL 360
Category: otc | Type: HUMAN OTC DRUG LABEL
Date: 20181103

ACTIVE INGREDIENTS: BENZALKONIUM CHLORIDE 0.44 g/354 mL
INACTIVE INGREDIENTS: WATER; SODIUM LAURETH SULFATE; COCAMIDOPROPYL BETAINE; GLYCERIN; SODIUM LAURYL SULFATE; PEG-150 DISTEARATE; CITRIC ACID MONOHYDRATE; METHYLCHLOROISOTHIAZOLINONE; METHYLISOTHIAZOLINONE; FD&C YELLOW NO. 5; FD&C RED NO. 40

KITCHEN LEMON ZEST Antibacterial Foaming Hand Soap

Drug Facts

Active ingredients Benzalkonium Chloride 0.13%

Purpose Antibacterial

INDICATIONS AND USAGE

Uses for hand washing to decrease bacteria on the skin.

Warnings For external use only.

When using this product avoid contact with eyes. In case of eye contact, flush with clean water.

Stop use and ask a doctor if irritation and redness develops.

Keep out of reach of children. If swallowed, get medical help or contact a Poison Control Center right away.

DOSAGE AND ADMINISTRATION

Directions ■ pump into hands ■ lather vigorously for at
least 15 seconds ■ rinse and dry thoroughly.

Inactive ingredients Water, Sodium Laureth Sulfate,
Cocamidopropyl Betaine, Glycerin, Sodium Lauryl Sulfate, PEG-150
Distearate, Fragrance, Citric Acid, Methylchloroisothiazolinone,
Methylisothiazolinone, FD&C Yellow No. 5, FD&C Red No. 40

Principal Display Package

719 Walnut®

Avenue

KITCHEN
LEMON ZEST

Antibacterial

Foaming Hand Soap

12 FL OZ (354 mL)

719 Walnut®

Avenue

KITCHEN
LEMON ZEST

Distributed by: Wal-Mart Stores, Inc. Bentonville, AR 72716

3-29500-00199-8

Made in China

↓Product Package↓

KITCHEN LEMON ZEST by Wal-Mart Stores, Inc.

res